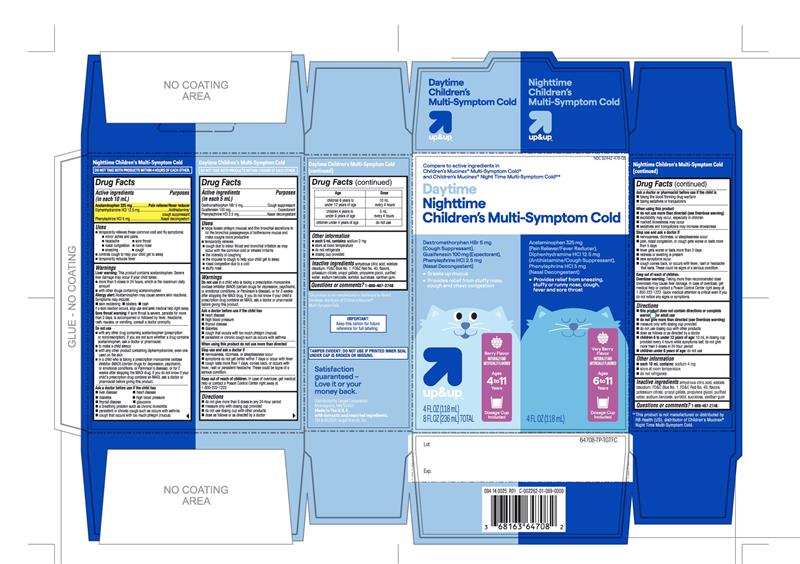 DRUG LABEL: up and up Daytime Nighttime Childrens Multi Symptom Cold
NDC: 82442-476 | Form: KIT | Route: ORAL
Manufacturer: Target Corporation
Category: otc | Type: HUMAN OTC DRUG LABEL
Date: 20251120

ACTIVE INGREDIENTS: DEXTROMETHORPHAN HYDROBROMIDE 5 mg/5 mL; GUAIFENESIN 100 mg/5 mL; PHENYLEPHRINE HYDROCHLORIDE 2.5 mg/5 mL; ACETAMINOPHEN 325 mg/10 mL; DIPHENHYDRAMINE HYDROCHLORIDE 12.5 mg/10 mL; PHENYLEPHRINE HYDROCHLORIDE 5 mg/10 mL
INACTIVE INGREDIENTS: ANHYDROUS CITRIC ACID; EDETATE DISODIUM; FD&C BLUE NO. 1; FD&C RED NO. 40; POTASSIUM CITRATE; PROPYL GALLATE; PROPYLENE GLYCOL; WATER; SODIUM BENZOATE; SORBITOL; SUCRALOSE; XANTHAN GUM; ANHYDROUS CITRIC ACID; EDETATE DISODIUM; FD&C BLUE NO. 1; FD&C RED NO. 40; POTASSIUM CITRATE; PROPYL GALLATE; PROPYLENE GLYCOL; WATER; SODIUM BENZOATE; SORBITOL; SUCRALOSE; XANTHAN GUM

Up&up Daytime Nighttime Children's Multi Symptom Cold Drug Facts

Day Time Multi-Symptom Cold

DO NOT TAKE BOTH PRODUCTS WITHIN 4 HOURS OF EACH OTHER

Drug Facts

ACTIVE INGREDIENT

PURPOSE

Active ingredients (in each 5 mL) | Purposes
Dextromethorphan HBr 5 mg | Cough suppressant
Guaifenesin 100 mg | Expectorant
Phenylephrine HCl 2.5 mg | Nasal decongestant

Uses

- helps loosen phlegm (mucus) and thin bronchial secretions to rid the bronchial passageways of bothersome mucus and make coughs more productive
- temporarily relieves:
  - cough due to minor throat and bronchial irritation as may occur with the common cold or inhaled irritants
  - the intensity of coughing
  - the impulse to cough to help your child get to sleep
  - nasal congestion due to a cold
  - stuffy nose

Warnings

DO NOT USE

Do not usein a child who is taking a prescription monoamine oxidase inhibitor (MAOI) (certain drugs for depression, psychiatric, or emotional conditions, or Parkinson's disease), or for 2 weeks after stopping the MAOI drug. If you do not know if your child's prescription drug contains an MAOI, ask a doctor or pharmacist before giving this product.

Ask a doctor before use if the child has

- heart disease
- high blood pressure
- thyroid disease
- diabetes
- cough that occurs with too much phlegm (mucus)
- persistent or chronic cough such as occurs with asthma

WHEN USING

When using this productdo not use more than directed

Stop use and ask a doctor if

- nervousness, dizziness or sleeplessness occur
- symptoms do not get better within 7 days or occur with fever
- cough lasts more than 7 days, comes back, or occurs with fever, rash, or persistent headache. These could be signs of a serious condition.

Keep out of reach of children.In case of overdose, get medical help or contact a Poison Control Center right away at 1-800-222-1222.

Directions

- do not give more than 6 doses in any 24-hour period
- measure only with dosing cup provided
- do not use dosing cup with other products
- dose as follows or as directed by a doctor

Age | Dose
children 6 years to under 12 years | 10 mL every 4 hours
children 4 years to under 6 years | 5 mL every 4 hours
children under 4 years | do not use

Other information

- each 5 mL contains:sodium 2 mg
- store at room temperature
- do not refrigerate
- dosing cup provided

Inactive ingredients

anhydrous citric acid, edetate disodium, FD&C Blue No.1, FD&C Red #40, flavors, potassium citrate, propyl gallate, propylene glycol, purified water, sodium benzoate, sorbitol, sucralose, xanthan gum

Questions or comments?

1-866-467-2748

Nighttime Children’s Multi-Symptom Cold

DO NOT TAKE BOTH PRODUCTS WITHIN 4 HOURS OF EACH OTHER

Drug Facts

ACTIVE INGREDIENT

PURPOSE

Active ingredients (in each 10 mL) | Purposes
Acetaminophen 325 mg | Pain reliever/fever reducer
Diphenhydramine HCl 12.5 mg | Antihistamine/cough suppressant
Phenylephrine HCl 5 mg | Nasal decongestant

Uses

- temporarily relieves these common cold and flu symptoms:
  - minor aches and pains
  - headache
  - sore throat
  - nasal congestion
  - runny nose
  - sneezing
  - cough
- controls cough to help your child get to sleep
- temporarily reduces fever

Warnings

Liver warning

This product contains acetaminophen. Severe liver damage may occur if your child takes:

- more than 5 doses in 24 hours, which is the maximum daily amount
- with other drugs containing acetaminophen

Allergy alert:Acetaminophen may cause severe skin reactions.

Symptoms may include:

- Skin reddening
- Blisters
- Rash

Sore throat warning:if sore throat is severe, persists for more than 2 days, is accompanied or followed by fever, headache, rash, nausea, or vomiting, consult a doctor promptly.

Do not use

- with any other drug containing acetaminophen (prescription or nonprescription). If you are not sure whether a drug contains acetaminophen, ask a doctor or pharmacist.
- to make a child sleepy
- with any other drug containing diphenhydramine, even one used on the skin
- in a child who is taking a prescription monoamine oxidase inhibitor (MAOI) (certain drugs for depression, psychiatric, or emotional conditions, or Parkinson's disease), or for 2 weeks after stopping the MAOI drug. If you do not know if your child's prescription drug contains an MAOI, ask a doctor or pharmacist before giving this product.

Ask a doctor before use if your child has

- liver disease
- heart disease
- diabetes
- high blood pressure
- thyroid disease
- glaucoma
- a breathing problem such as chronic bronchitis
- persistent or chronic cough such as occurs with asthma
- cough that occurs with too much phlegm (mucus)

Ask a doctor or pharmacist before use if your child is

- taking the blood thinning drug warfarin
- taking sedatives or tranquilizers

When using this product

- do not use more than directed (see Overdose warning)
- excitability may occur, especially in children
- marked drowsiness may occur
- sedatives and tranquilizers may increase drowsiness

Stop use and ask a doctor if

- nervousness, dizziness, or sleeplessness occur
- pain, nasal congestion, or cough gets worse or lasts more than 5 days
- fever gets worse, or lasts more than 3 days
- redness or swelling is present
- new symptoms occur
- cough comes back, or occurs with fever, rash, or headache that lasts. These could be signs of a serious condition.

Keep out of reach of children.

Overdose warning

Taking more than the recommended dose (overdose) may cause liver damage. In case of overdose, get medical help or contact a Poison Control Center right away. Quick medical attention is critical for adults as well as for children even if you do not notice any signs or symptoms.

Directions

- this product does not contain directions or complete warnings for adult use
- do not give more than directed (see Overdose warning)
- measure only with dosing cup provided
- do not use dosing cup with other products
- dose as follows or as directed by a doctor
- children 6 to under 12 years of age: 10 mL in dosing cup provided every 4 hours; do not give more than 5 doses in any 24-hour period
- children under 6 years of age: do not use

Other information

- each 10 mL contains:sodium 4 mg
- store at room temperature
- do not refrigerate

Inactive ingredients

anhydrous citric acid, edetate disodium, FD&C Blue #1, FD&C Red #40, flavors, potassium citrate, propyl gallate, propylene glycol, purified water, sodium benzoate, sorbitol, sucralose, xanthan gum

Questions?

1-866-467-2748.

Dist. by: Target Corporation

Minneapolis, MN 55403

Made In the U.S.A.

With domestic and imported ingredients.

TM & © 2024 Target Brands, Inc.

PRINCIPAL DISPLAY PANEL - Kit Carton

VALUE
PACK

Compare to active ingredients in Children’s Mucinex® Multi-Symptom Cold* and Children’s Mucinex® Nighttime Multi-Symptom Cold**

NDC 82442-476-08

Daytime Nighttime Children’s Multi-Symptom Cold

Dextromethorphan HBr 5 mg (Cough Suppressant)
Guaifenesin 100 mg (Expectorant)
Phenylephrine HCl 2.5 mg (Nasal Decongestant)

- Breaks up Mucus
- Provides relief from stuffy nose, cough and chest congestion

Age 4 to 11 Years

Dosage Cup Included

Berry Flavor

NATURALLY AND ARTIFICIALLY FLAVORED

4 FL OZ (118 mL)

NIGHTTIME

Multi-Symptom
Cold
Acetaminophen 325 mg(Pain Reliever/Fever Reducer)
Diphenhydramine HCl 12.5 mg (Antihistamine/Cough Suppressant)
Phenylephrine HCl 5 mg (Nasal Decongestant)

- Provides relief from sneezing, stuffy or runny nose, cough, fever and sore throat

Very Berry Flavor

NATURALLY AND ARTIFICIALLY FLAVORED

Ages 6 to 11 years

Dosage Cup Included

4 FL OZ (118 mL)

8 FL OZ (236 mL) TOTAL

* This product is not manufactured or distributed by RB Health (US), distributor of Children’s Mucinex® Multi-Symptom Cold.

**This product is not manufactured or distributed by RB Health (US), distributor of Children’s Mucinex® Nighttime Multi-Symptom Cold.

TAMPER EVIDENT: DO NOT USE IF PRINTED INNER SEAL UNDER CAP IS BROKEN OR MISSING.

Important: Keep this carton for future reference for full labeling.